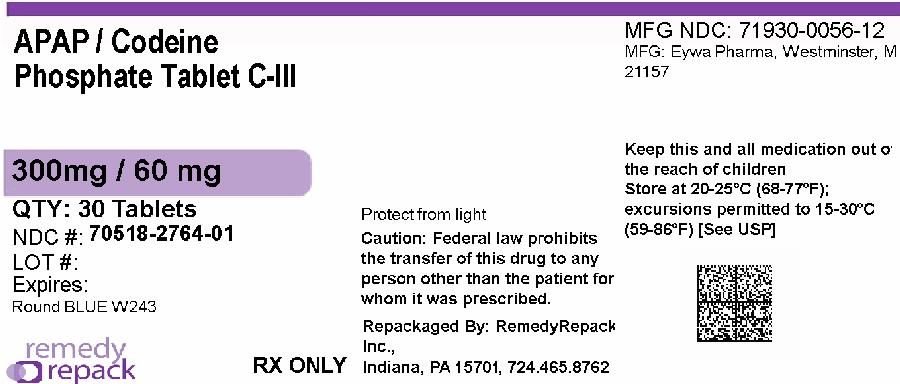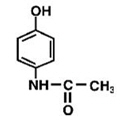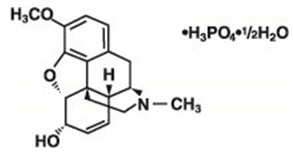 DRUG LABEL: ACETAMINOPHEN AND CODEINE PHOSPHATE
NDC: 70518-2764 | Form: TABLET
Manufacturer: REMEDYREPACK INC.
Category: prescription | Type: HUMAN PRESCRIPTION DRUG LABEL
Date: 20260211
DEA Schedule: CIII

ACTIVE INGREDIENTS: ACETAMINOPHEN 300 mg/1 1; CODEINE PHOSPHATE 60 mg/1 1
INACTIVE INGREDIENTS: CELLULOSE, MICROCRYSTALLINE; CROSCARMELLOSE SODIUM; SILICON DIOXIDE; MAGNESIUM STEARATE; STARCH, CORN; POVIDONE; CROSPOVIDONE; STEARIC ACID; FD&C BLUE NO. 1

BOXED WARNING

WARNING: SERIOUS AND LIFE-THREATENING RISKS FROM USE OF ACETAMINOPHEN AND CODEINE PHOSPHATE TABLETS, USP

Addiction, Abuse, and Misuse

Because the use of acetaminophen and codeine phosphate tablets exposes patients and other users to the risks of opioid addiction, abuse, and misuse, which can lead to overdose and death, assess each patient’s risk prior to prescribing and reassess all patients regularly for the development of these behaviors and conditions [see Warnings].

Life-Threatening Respiratory Depression

Serious, life-threatening, or fatal respiratory depression may occur with use of acetaminophen and codeine phosphate tablets, especially during initiation or following a dosage increase. To reduce the risk of respiratory depression, proper dosing and titration of acetaminophen and codeine phosphate tablets are essential [see Warnings].

Accidental Ingestion

Accidental ingestion of even one dose of acetaminophen and codeine phosphate tablets, especially by children, can result in a fatal overdose of acetaminophen and codeine phosphate [see Warnings].

Risks From Concomitant Use with Benzodiazepines Or Other CNS Depressants

Concomitant use of opioids with benzodiazepines or other central nervous system (CNS) depressants, including alcohol, may result in profound sedation, respiratory depression, coma, and death. Reserve concomitant prescribing of acetaminophen and codeine phosphate tablets and benzodiazepines or other CNS depressants for use in patients for whom alternative treatment options are inadequate [see Warnings, Drug Interactions].

Neonatal Opioid Withdrawal Syndrome (NOWS)

Advise pregnant women using opioids for an extended period of time of the risk of Neonatal Opioid Withdrawal Syndrome, which may be life-threatening if not recognized and treated. Ensure that management by neonatology experts will be available at delivery [see Warnings].

Opioid Analgesic Risk Evaluation and Mitigation Strategy (REMS)

Healthcare providers are strongly encouraged to complete a REMS-compliant education program and to counsel patients and caregivers on serious risks, safe use, and the importance of reading the Medication Guide with each prescription [see Warnings].

Ultra-Rapid Metabolism of Codeine and Other Risk Factors for Life-Threatening Respiratory Depression in Children

Life-threatening respiratory depression and death have occurred in children who received codeine. Most of the reported cases occurred following tonsillectomy and/or adenoidectomy and many of the children had evidence of being ultra-rapid metabolizers of codeine due to a cytochrome P450 (CYP) 2D6 polymorphism (see WARNINGS, PRECAUTIONS; Information for Patients /Caregivers, Nursing Mothers). Acetaminophen and codeine phosphate tablets are contraindicated in children younger than 12 years of age and in children younger than 18 years of age following tonsillectomy and/or adenoidectomy (see CONTRAINDICATIONS). Avoid the use of acetaminophen and codeine phosphate tablets in adolescents 12 to 18 years of age who have other risk factors that may increase their sensitivity to the respiratory depressant effects of codeine (see WARNINGS, PRECAUTIONS).

Interactions with Drugs Affecting Cytochrome P450 Isoenzymes

The effects of concomitant use or discontinuation of CYP3A4 inducers, CYP3A4inhibitors, or CYP2D6 inhibitors with codeine are complex. Use of CYP3A4inducers, CYP3A4 inhibitors, or CYP2D6 inhibitors with acetaminophen and codeine phosphate tablets requires careful consideration of the effects on the parent drug, codeine, and the active metabolite, morphine (see WARNINGS, PRECAUTIONS: DRUG INTERACTIONS).

Hepatotoxicity

Acetaminophen has been associated with cases of acute liver failure, at times resulting in liver transplant and death. Most of the cases of liver injury are associated with the use of acetaminophen at doses that exceed 4,000 milligrams per day, and often involve more than one acetaminophen-containing product (see WARNINGS).

DESCRIPTION

Acetaminophen and Codeine Phosphate Tablets, USP are supplied in tablet form for oral administration.
Acetaminophen, 4'-hydroxyacetanilide, a slightly bitter, white, odorless, crystalline powder, is a non-opiate, non-salicylate analgesic and antipyretic. It has the following structural formula:
C8H9NO2 M.W. 151.16
Codeine phosphate, 7,8-didehydro-4, 5α-epoxy-3-methoxy-17-methylmorphinan-6α-ol phosphate (1:1) (salt) hemihydrate, a white crystalline powder, is a narcotic analgesic and antitussive. It has the following structural formula:
C18H21NO3H3PO4½H2O M.W. 406.37
Each Acetaminophen and Codeine Phosphate Tablet USP, 300 mg/15 mg contains:
Acetaminophen USP………………..…300 mg
Codeine Phosphate USP……………….15 mg
Each Acetaminophen and Codeine Phosphate Tablet USP, 300 mg/30 mg contains:
Acetaminophen USP……………..……300 mg
Codeine Phosphate USP……………….30 mg
Each Acetaminophen and Codeine Phosphate Tablet USP, 300 mg/60 mg contains:
Acetaminophen USP……………..……300 mg
Codeine Phosphate USP……………….60 mg
In addition, each tablet contains the following inactive ingredients:
colloidal silicon dioxide, corn starch, croscarmellose sodium, crospovidone, magnesium stearate, microcrystalline cellulose, povidone, stearic acid, FD&C Red #40 aluminum lake (300 mg/15 mg only), and FD&C Blue#1 aluminum lake (300 mg/60 mg only).

CLINICAL PHARMACOLOGY

Mechanism of ActionCodeine is an opioid agonist relatively selective for the mu-opioid receptor, but with a much weaker affinity than morphine. The analgesic properties of codeine have been speculated to come from its conversion to morphine, although the exact mechanism of analgesic action remains unknown.
The precise mechanism of the analgesic properties of acetaminophen is not established but is thought to involve central actions.
PharmacodynamicsEffects on the Central Nervous System
Codeine produces respiratory depression by direct action on brain stem respiratory centers. The respiratory depression involves a reduction in the responsiveness of the brain stem respiratory centers to both increases in carbon dioxide tension and electrical stimulation.
Codeine causes miosis, even in total darkness. Pinpoint pupils are a sign of opioid overdose but are not pathognomonic (e.g., pontine lesions of hemorrhagic or ischemic origins may produce similar findings). Marked mydriasis rather than miosis may be seen due to hypoxia in overdose situations.
Effects on the Gastrointestinal Tract and Other Smooth Muscle
Codeine causes a reduction in motility associated with an increase in smooth muscle tone in the antrum of the stomach and duodenum. Digestion of food in the small intestine is delayed and propulsive contractions are decreased. Propulsive peristaltic waves in the colon are decreased, while tone may be increased to the point of spasm, resulting in constipation. Other opioid-induced effects may include a reduction in biliary and pancreatic secretions, spasm of sphincter of Oddi, and transient elevations in serum amylase, and opioid-induced esophageal dysfunction (OIED).
Effects on the Cardiovascular System
Codeine produces peripheral vasodilation which may result in orthostatic hypotension or syncope. Manifestations of histamine release and/or peripheral vasodilation may include pruritus, flushing, red eyes, sweating, and/or orthostatic hypotension.
Effects on the Endocrine System
Opioids inhibit the secretion of adrenocorticotropic hormone (ACTH), cortisol, and luteinizing hormone (LH) in humans (see ADVERSEREACTIONS). They also stimulate prolactin, growth hormone (GH) secretion, and pancreatic secretion of insulin and glucagon.

Use of opioids for an extended period of time may influence the hypothalamic-pituitary-gonadal axis, leading to androgen deficiency that may manifest as low libido, impotence, erectile dysfunction, amenorrhea, or infertility. The causal role of opioids in the clinical syndrome of hypogonadism is unknown because the various medical, physical, lifestyle, and psychological stressors that may influence gonadal hormone levels have not been adequately controlled for in studies conducted to date (see ADVERSE REACTIONS).

Effects on the Immune System
Opioids have been shown to have a variety of effects on components of the immune system. The clinical significance of these findings is unknown. Overall, the effects of opioids appear to be modestly immunosuppressive.
Concentration-Efficacy Relationships
The minimum effective analgesic concentration will vary widely among patients, especially among patients who have been previously treated with opioid agonists. The minimum effective analgesic concentration of codeine for any individual patient may increase over time due to an increase in pain, the development of a new pain syndrome, and/or the development of analgesic tolerance (see DOSAGE AND ADMINISTRATION).

Concentration-Adverse Reaction Relationships
There is a relationship between increasing codeine plasma concentration and increasing frequency of dose-related opioid adverse reactions such as nausea, vomiting, CNS effects, and respiratory depression. In opioid-tolerant patients, the situation may be altered by the development of tolerance to opioid-related adverse reactions (see DOSAGE AND ADMINISTRATION).

Pharmacokinetics

The behavior of the individual components is described below.
Codeine
Codeine is rapidly absorbed from the gastrointestinal tract. It is rapidly distributed from the intravascular spaces to the various body tissues, with preferential uptake by parenchymatous organs such as the liver, spleen, and kidney. Codeine crosses the blood-brain barrier and is found in fetal tissue and breast milk. The plasma concentration does not correlate with brain concentration or relief of pain. Codeine is about 7–25% bound to plasma proteins and does not accumulate in body tissues.
About 70 to 80% of the administered dose of codeine is metabolized by conjugation with glucuronic acid to codeine-6-glucuronide (C6G) and via O-demethylation to morphine (about 5 to 10%) and N-demethylation to norcodeine (about 10%) respectively. UDP-glucuronosyltransferase (UGT) 2B7 and 2B4 are the major enzymes mediating glucuronidation of codeine to C6G. CYP2D6 is the major enzyme responsible for conversion of codeine to morphine and CYP3A4 is the major enzyme mediating conversion of codeine to norcodeine. Morphine and norcodeine are further metabolized by conjugation with glucuronic acid. The glucuronide metabolites of morphine are morphine-3-glucuronide (M3G) and morphine-6-glucuronide (M6G). Morphine and M6G are known to have analgesic activity in humans. The analgesic activity of C6G in humans is unknown. Norcodeine and M3G are generally not considered to possess analgesic properties.
The plasma half-life is about 2.9 hours. The elimination of codeine is primarily via the kidneys, and about 90% of an oral dose is excreted by the kidneys within 24 hours of dosing. The urinary secretion products consist of free and glucuronide conjugated codeine (about 70%), free and conjugated norcodeine (about 10%), free and conjugated morphine (about 10%), normorphine (4%), and hydrocodone (1%). The remainder of the dose is excreted in the feces.
At therapeutic doses, the analgesic effect reaches a peak within 2 hours and persists between 4 and 6 hours.
Acetaminophen
Acetaminophen is rapidly absorbed from the gastrointestinal tract and is distributed throughout most body tissues. A small fraction (10–25%) of acetaminophen is bound to plasma proteins. The plasma half-life is 1.25 to 3 hours but may be increased by liver damage and following overdosage. Elimination of acetaminophen is principally by liver metabolism (conjugation) and subsequent renal excretion of metabolites. Acetaminophen is primarily metabolized in the liver by first-order kinetics and involves three principal separate pathways: conjugation with glucuronide; conjugation with sulfate; and oxidation via the cytochrome, P450-dependent, mixed-function oxidase enzyme pathway to form a reactive intermediate metabolite, which conjugates with glutathione and is then further metabolized to form cysteine and mercapturic acid conjugates. The principal cytochrome P450 isoenzyme involved appears to be CYP2E1, with CYP1A2 and CYP3A4 as additional pathways. Approximately 85% of an oral dose appears in the urine within 24 hours of administration, most as the glucuronide conjugate, with small amounts of other conjugates and unchanged drug.
See OVERDOSAGEfor toxicity information.

INDICATIONS AND USAGE

Acetaminophen and codeine phosphate tablets are indicated for the management of mild to moderate pain, where treatment with an opioid is appropriate and for which alternative treatments are inadequate.
Limitations of Use

Because of the risks of addiction, abuse, misuse, overdose, and death, which can occur at any dosage or duration and persist over the course of therapy, (see WARNINGS), reserve opioid analgesics, including codeine phosphate for use in patients for whom alternative treatment options are ineffective, not tolerated, or would be otherwise inadequate to provide sufficient management of pain.

CONTRAINDICATIONS

Acetaminophen and codeine phosphate tablets are contraindicated for:
• All children younger than 12 years of age (see WARNINGS)
• Post-operative management in children younger than 18 years of age following tonsillectomy and/or adenoidectomy (see WARNINGS).

Acetaminophen and codeine phosphate tablets are contraindicated in patients with:
• Significant respiratory depression (see WARNINGS).
• Acute or severe bronchial asthma in an unmonitored setting or in the absence of resuscitative equipment (see WARNINGS).
• Concurrent use of monoamine oxidase inhibitors (MAOIs) or use of MAOIs within the last 14 days (see WARNINGS).
• Known or suspected gastrointestinal obstruction, including paralytic ileus (see WARNINGS).
• Hypersensitivity to codeine, acetaminophen, or any of the ingredients (e.g., anaphylaxis) (see WARNINGS).

WARNINGS

Addiction, Abuse, and Misuse

Acetaminophen and codeine phosphate tablets contain codeine. Codeine in combination with acetaminophen, is a Schedule III controlled substance. As an opioid, acetaminophen and codeine phosphate tablets expose users to the risks of addiction, abuse, and misuse (see DRUG ABUSE and DEPENDENCE).
Although the risk of addiction in any individual is unknown, it can occur in patients appropriately prescribed acetaminophen and codeine phosphate tablets. Addiction can occur at recommended dosages and if the drug is misused or abused. The risk of opioid-related overdose or overdose-related death is increased with higher opioid doses, and this risk persists over the course of therapy. In postmarketing studies, addiction, abuse, misuse, and fatal and non-fatal opioid overdose were observed in patients with long-term opioid use [ADVERSE REACTIONS] .

Assess each patient’s risk for opioid addiction, abuse, or misuse prior to prescribing acetaminophen and codeine phosphate tablets, and reassess all patients receiving acetaminophen and codeine phosphate tablets for the development of these behaviors and conditions. Risks are increased in patients with a personal or family history of substance abuse (including drug or alcohol abuse or addiction) or mental illness (e.g., major depression). The potential for these risks should not, however, prevent the proper management of pain in any given patient. Patients at increased risk may be prescribed opioids such as acetaminophen and codeine phosphate tablets, but use in such patients necessitates intensive counseling about the risks and proper use of acetaminophen and codeine phosphate tablets along with frequent reevaluation for signs of addiction, abuse, and misuse. Consider recommending or prescribing an opioid overdose reversal agent (see WARNINGS, Life-Threatening Respiratory Depression; DOSAGE AND ADMINISTRATION, Patient Access to Naloxone for the Emergency Treatment of Opioid Overdose).
Opioids are sought for nonmedical use and are subject to diversion from legitimate prescribed use. Consider these risks when prescribing or dispensing acetaminophen and codeine phosphate tablets. Strategies to reduce these risks include prescribing the drug in the smallest appropriate quantity and advising the patient on careful storage of the drug during the course of treatment and proper disposal of unused drug [see PRECAUTIONS, Information for Patients/Caregivers]. Contact local state professional licensing board or state-controlled substances authority for information on how to prevent and detect abuse or diversion of this product.

Life-Threatening Respiratory Depression

Serious, life-threatening, or fatal respiratory depression has been reported with the use of opioids, even when used as recommended. Respiratory depression, if not immediately recognized and treated, may lead to respiratory arrest and death. Management of respiratory depression may include close observation, supportive measures, and use of opioid overdose reversal agents, depending on the patient’s clinical status (see OVERDOSAGE). Carbon dioxide (CO2) retention from opioid-induced respiratory depression can exacerbate the sedating effects of opioids.
While serious, life-threatening, or fatal respiratory depression can occur at any time during the use of acetaminophen and codeine phosphate tablets, the risk is greatest during the initiation of therapy or following a dosage increase of acetaminophen and codeine phosphate tablets.
To reduce the risk of respiratory depression, proper dosing and titration of acetaminophen and codeine phosphate tablets are essential (see DOSAGE AND ADMINISTRATION). Overestimating the acetaminophen and codeine phosphate tablets dosage when converting patients from another opioid product can result in a fatal overdose with the first dose.
Accidental ingestion of acetaminophen and codeine phosphate tablets, especially by children, can result in respiratory depression and death due to an overdose of codeine.
Educate patients and caregivers on how to recognize respiratory depression and emphasize the importance of calling 911 or getting emergency medical help right away in the event of a known or suspected overdose (see PRECAUTIONS, Information for Patients/Caregivers).
Opioids can cause sleep-related breathing disorders including central sleep apnea (CSA) and sleep-related hypoxemia. Opioid use increases the risk of CSA in a dose-dependent fashion. In patients who present with CSA, consider decreasing the opioid dosage using best practices for opioid taper (see DOSAGE AND ADMINISTRATION).
Patient Access to an Opioid Overdose Reversal Agent for the Emergency Treatment of Opioid Overdose

Inform patients and caregivers about opioid overdose reversal agents (e.g., naloxone, nalmefene). Discuss the importance of having access to an opioid overdose reversal agent, especially if the patient has risk factors for overdose (e.g., concomitant use of CNS depressants, a history of opioid use disorder, or prior opioid overdose) or if there are household members (including children) or other close contacts at risk for accidental ingestion or opioid overdose. The presence of risk factors for overdose should not prevent the management of pain in any patient [see WARNINGS].

Discuss the options for obtaining an opioid overdose reversal agent (e.g., prescription, over-the-counter, or as part of a community-based program).

There are important differences among the opioid overdose reversal agents, such as route of administration, product strength, approved patient age range, and pharmacokinetics. Be familiar with these differences, as outlined in the approved labeling for those products, prior to recommending or prescribing such an agent.

Educate patients and caregivers on how to recognize respiratory depression, and how to use an opioid overdose reversal agent for the emergency treatment of opioid overdose. Emphasize the importance of calling 911 or getting emergency medical help, even if an opioid overdose reversal agent is administered [see WARNINGS, OVERDOSAGE].
Risks from Concomitant Use with Benzodiazepines and Other CNS Depressants

Profound sedation, respiratory depression, coma, and death may result from the concomitant use of acetaminophen and codeine phosphate tablets with benzodiazepines and/or other CNS depressants, including alcohol (e.g., non-benzodiazepine sedatives/hypnotics, anxiolytics, tranquilizers, muscle relaxants, general anesthetics, antipsychotics, gabapentinoids [gabapentin or pregabalin], and other opioids). Because of these risks, reserve concomitant prescribing of these drugs for use in patients for whom alternative treatment options are inadequate.
Observational studies have demonstrated that concomitant use of opioid analgesics and benzodiazepines increases the risk of drug-related mortality compared to use of opioid analgesics alone. Because of similar pharmacological properties, it is reasonable to expect similar risk with the concomitant use of other CNS depressant drugs with opioid analgesics (see PRECAUTIONS; Drug Interactions).
If the decision is made to prescribe a benzodiazepine or other CNS depressant concomitantly with an opioid analgesic, prescribe the lowest effective dosages and minimum durations of concomitant use. In patients already receiving an opioid analgesic, prescribe a lower initial dose of the benzodiazepine or other CNS depressant than indicated in the absence of an opioid, and titrate based on clinical response. If an opioid analgesic is initiated in a patient already taking a benzodiazepine or other CNS depressant, prescribe a lower initial dose of the opioid analgesic, and titrate based on clinical response. Inform patients and caregivers of this potential interaction, educate them on the signs and symptoms of respiratory depression (including sedation).

If concomitant use is warranted, consider recommending or prescribing an opioid overdose reversal agent (see WARNINGS, Life-Threatening Respiratory Depression; DOSAGE AND ADMINISTRATION, Patient Access to Naloxone for the Emergency Treatment of Opioid Overdose).
Advise both patients and caregivers about the risks of respiratory depression and sedation when acetaminophen and codeine phosphate tablets are used with benzodiazepines or other CNS depressants (including alcohol and illicit drugs). Advise patients not to drive or operate heavy machinery until the effects of concomitant use of the benzodiazepine or other CNS depressant have been determined. Screen patients for risk of substance use disorders, including opioid abuse and misuse, and warn them of the risk for overdose and death associated with the use of additional CNS depressants including alcohol and illicit drugs (see PRECAUTIONS; Drug Interactions, Information for Patients/Caregivers).

Neonatal Opioid Withdrawal Syndrome

Use of acetaminophen and codeine phosphate tablets for an extended period of time during pregnancy can result in withdrawal in the neonate. Neonatal opioid withdrawal syndrome, unlike opioid withdrawal syndrome in adults, may be life-threatening if not recognized and treated, and requires management according to protocols developed by neonatology experts. Observe newborns for signs of neonatal opioid withdrawal syndrome and manage accordingly. Advise pregnant women using opioids for an extended period of time of the risk of neonatal opioid withdrawal syndrome and ensure that appropriate treatment will be available (see PRECAUTIONS, Information for Patients /Caregivers, Pregnancy).

Opioid Analgesic Risk Evaluation and Mitigation Strategy (REMS)

To ensure that the benefits of opioid analgesics outweigh the risks of addiction, abuse, and misuse, the Food and Drug Administration (FDA) has required a Risk Evaluation and Mitigation Strategy (REMS) for these products. Under the requirements of the REMS, drug companies with approved opioid analgesic products must make REMS-compliant education programs available to healthcare providers. Healthcare providers are strongly encouraged to do all of the following:
• Complete a REMS-compliant education program offered by an accredited provider of continuing education (CE) or another education program that includes all the elements of the FDA Education Blueprint for Health Care Providers Involved in the
Management or Support of Patients with Pain.
• Discuss the safe use, serious risks, and proper storage and disposal of opioid analgesics with patients and/or their caregivers every time these medicines are prescribed. The Patient Counseling Guide (PCG) can be obtained at this link: www.fda.gov/OpioidAnalgesicREMSPCG.
• Emphasize to patients and their caregivers the importance of reading the Medication Guide that they will receive from their pharmacist every time an opioid analgesic is dispensed to them.
• Consider using other tools to improve patient, household, and community safety, such as patient-prescriber agreements that reinforce patient-prescriber responsibilities.

To obtain further information on the opioid analgesic REMS and for a list of accredited REMS CME/CE, call 800-503-0784, or log on to www.opioidanalgesicrems.com. The FDA Blueprint can be found at www.fda.gov/OpioidAnalgesicREMSBlueprint.

Ultra-Rapid Metabolism of Codeine and Other Risk Factors for Life-Threatening Respiratory Depression in Children

Life-threatening respiratory depression and death have occurred in children who received codeine. Codeine is subject to variability in metabolism based upon CYP2D6 genotype (described below), which can lead to an increased exposure to the active metabolite morphine. Based upon post-marketing reports, children younger than 12 years of age appear to be more susceptible to the respiratory depressant effects of codeine, particularly if there are risk factors for respiratory depression. For example, many reported cases of death occurred in the post-operative period following tonsillectomy and/or adenoidectomy, and many of the children had evidence of being ultra-rapid metabolizers of codeine. Furthermore, children with obstructive sleep apnea who are treated with codeine for post-tonsillectomy and/or adenoidectomy pain may be particularly sensitive to its respiratory depressant effects

Because of the risk of life-threatening respiratory depression and death:
• Acetaminophen and codeine phosphate tablets are contraindicated for all children younger than 12 years of age (see CONTRAINDICATIONS).
• Acetaminophen and codeine phosphate tablets are contraindicated for post-operative management in pediatric patients younger than 18 years of age following tonsillectomy and/or adenoidectomy (see CONTRAINDICATIONS).
• Avoid the use of acetaminophen and codeine phosphate tablets in adolescents 12 to 18 years of age who have other risk factors that may increase their sensitivity to the respiratory depressant effects of codeine unless the benefits outweigh the risks. Risk factors include conditions associated with hypoventilation, such as post-operative status, obstructive sleep apnea, obesity, severe pulmonary disease, neuromuscular disease, and concomitant use of other medications that cause respiratory depression (see WARNINGS).
• As with adults, when prescribing codeine for adolescents, healthcare providers should choose the lowest effective dose for the shortest period of time and inform patients and caregivers about these risks and the signs of morphine overdose (see OVERDOSAGE).
Nursing Mothers

At least one death was reported in a nursing infant who was exposed to high levels of morphine in breast milk because the mother was an ultra-rapid metabolizer of codeine. Breastfeeding is not recommended during treatment with acetaminophen and codeine phosphate tablets.
CYP2D6 Genetic Variability: Ultra-Rapid Metabolizers
Some individuals may be ultra-rapid metabolizers because of a specific CYP2D6 genotype (e.g., gene duplications denoted as *1/*1×N or *1/*2×N). The prevalence of this CYP2D6 phenotype varies widely and has been estimated at 1 to 10% for Whites (European, North American), 3 to 4% for Blacks (African Americans), 1 to 2% for East Asians (Chinese, Japanese, Korean), and may be greater than 10% in certain racial/ethnic groups (i.e., Oceanian, Northern African, Middle Eastern, Ashkenazi Jews, Puerto Rican). These individuals convert codeine into its active metabolite, morphine, more rapidly and completely than other people. This rapid conversion results in higher than expected serum morphine levels. Even at labeled dosage regimens, individuals who are ultra-rapid metabolizers may have life-threatening or fatal respiratory depression or experience signs of overdose (such as extreme sleepiness, confusion, or shallow breathing) (see OVERDOSAGE). Therefore, individuals who are ultra-rapid metabolizers should not use acetaminophen and codeine phosphate tablets.
Interactions with Drugs Affecting Cytochrome P450 Isoenzymes

The effects of concomitant use or discontinuation of CYP3A4 inducers, CYP3A4 inhibitors, or CYP2D6 inhibitors with codeine are complex. Use of CYP3A4 inducers, CYP3A4 inhibitors, or CYP2D6 inhibitors with acetaminophen and codeine phosphate tablets requires careful consideration of the effects on the parent drug, codeine, and the active metabolite, morphine.

CYP3A4 Interaction

The concomitant use of acetaminophen and codeine phosphate tablets with all CYP3A4 inhibitors, such as macrolide antibiotics (e.g., erythromycin), azole-antifungal agents (e.g., ketoconazole), and protease inhibitors (e.g., ritonavir) or discontinuation of a CYP3A4 inducer such as rifampin, carbamazepine, and phenytoin, may result in an increase in codeine plasma concentrations with subsequently greater metabolism by CYP2D6, resulting in greater morphine levels, which could increase or prolong adverse reactions and may cause potentially fatal respiratory depression.

The concomitant use of acetaminophen and codeine phosphate tablets with all CYP3A4 inducers or discontinuation of a CYP3A4 inhibitor may result in lower codeine levels, greater norcodeine levels, and less metabolism via CYP2D6 with resultant lower morphine levels. This may be associated with a decrease in efficacy, and in some patients, may result in signs and symptoms of opioid withdrawal.

Evaluate patients receiving acetaminophen and codeine phosphate tablets and any CYP3A4 inhibitor or inducer for signs and symptoms that may reflect opioid toxicity and opioid withdrawal when acetaminophen and codeine phosphate tablets are used in conjunction with inhibitors and inducers of CYP3A4 (see PRECAUTIONS, Drug Interactions).

If concomitant use of a CYP3A4 inhibitor is necessary or if a CYP3A4 inducer is discontinued, consider dosage reduction of acetaminophen and codeine phosphate tablets until stable drug effects are achieved. Evaluate patients at frequent intervals for respiratory depression and sedation.
If concomitant use of a CYP3A4 inducer is necessary or if a CYP3A4 inhibitor is discontinued, consider increasing the acetaminophen and codeine phosphate tablets dosage until stable drug effects are achieved. Evaluate for signs of opioid withdrawal (see PRECAUTIONS, Drug Interactions).
Risks of Concomitant Use or Discontinuation of CYP2D6 Inhibitors
The concomitant use of acetaminophen and codeine phosphate tablets with all CYP2D6 inhibitors (e.g., amiodarone, quinidine) may result in an increase in codeine plasma concentrations and a decrease in active metabolite morphine plasma concentration which could result in an analgesic efficacy reduction or symptoms of opioid withdrawal.

Discontinuation of a concomitantly used cytochrome P450 2D6 inhibitor may result in a decrease in codeine plasma concentration and an increase in active metabolite morphine plasma concentration which could increase or prolong adverse reactions and may cause potentially fatal respiratory depression.

Evaluate patients receiving acetaminophen and codeine phosphate tablets and any CYP2D6 inhibitor for signs and symptoms that may reflect opioid toxicity and opioid withdrawal when acetaminophen and codeine phosphate tablets are used in conjunction with inhibitors of CYP2D6.

If concomitant use with a CYP2D6 inhibitor is necessary, assess the patient for signs of reduced efficacy or opioid withdrawal and consider increasing the acetaminophen and codeine phosphate tablets dosage. After stopping use of a CYP2D6 inhibitor, consider reducing the acetaminophen and codeine phosphate tablets dosage and evaluate the patient at frequent intervals for signs and symptoms of respiratory depression or sedation (see PRECAUTIONS, Drug Interactions).
Hepatotoxicity

Acetaminophen has been associated with cases of acute liver failure, at times resulting in liver transplant and death. Most of the cases of liver injury are associated with the use of acetaminophen at doses that exceed 4,000 milligrams per day, and often involve more than one acetaminophen-containing product. The excessive intake of acetaminophen may be intentional to cause self-harm or unintentional as patients attempt to obtain more pain relief or unknowingly take other acetaminophen-containing products.

The risk of acute liver failure is higher in individuals with underlying liver disease and in individuals who ingest alcohol while taking acetaminophen.

Instruct patients to look for acetaminophen or APAP on package labels and not to use more than one product that contains acetaminophen. Instruct patients to seek medical attention immediately upon ingestion of more than 4,000 milligrams of acetaminophen per day, even if they feel well.

Opioid-Induced Hyperalgesia and Allodynia

Opioid-Induced Hyperalgesia (OIH) occurs when an opioid analgesic paradoxically causes an increase in pain, or an increase in sensitivity to pain. This condition differs from tolerance, which is the need for increasing doses of opioids to maintain a defined effect [see Dependence]. Symptoms of OIH include (but may not be limited to) increased levels of pain upon opioid dosage increase, decreased levels of pain upon opioid dosage decrease, or pain from ordinarily non-painful stimuli (allodynia). These symptoms may suggest OIH only if there is no evidence of underlying disease progression, opioid tolerance, opioid withdrawal, or addictive behavior.

Cases of OIH have been reported, both with short-term and longer-term use of opioid analgesics. Though the mechanism of OIH is not fully understood, multiple biochemical pathways have been implicated. Medical literature suggests a strong biologic plausibility between opioid analgesics and OIH and allodynia. If a patient is suspected to be experiencing OIH, carefully consider appropriately decreasing the dose of the current opioid analgesic, or opioid rotation (safely switching the patient to a different opioid moiety) [see Dosage and Administration; Warnings].
Life-Threatening Respiratory Depression in Patients with Chronic Pulmonary Disease or Elderly, Cachectic, or Debilitated PatientsThe use of acetaminophen and codeine phosphate tablets in patients with acute or severe bronchial asthma in an unmonitored setting or in the absence of resuscitative equipment is contraindicated.

Patients with Chronic Pulmonary Disease

Acetaminophen and codeine phosphate tablets -treated patients with significant chronic obstructive pulmonary disease or cor pulmonale, and those with a substantially compromised respiratory function, hypoxia, hypercapnia, or pre-existing respiratory depression are at increased risk of decreased respiratory drive including apnea, even at recommended dosages of acetaminophen and codeine phosphate tablets (see WARNINGS; Life- Threatening Respiratory Depression).

Elderly, Cachectic, or Debilitated Patients
Life-threatening respiratory depression is more likely to occur in elderly, cachectic, or debilitated patients because they may have altered pharmacokinetics, including clearance, compared to younger, healthier patients (see WARNINGS; Life-Threatening Respiratory Depression).

Regularly evaluate patients, particularly when initiating and titrating acetaminophen and codeine phosphate tablets and when acetaminophen and codeine phosphate tablets are given concomitantly with other drugs that depress respiration (see WARNINGS). Alternatively, consider the use of non-opioid analgesics in these patients.

Interaction with Monoamine Oxidase Inhibitors

Monoamine oxidase inhibitors (MAOIs) may potentiate the effects of morphine, codeine's active metabolite, including respiratory depression, coma, and confusion. Acetaminophen and codeine phosphate tablets should not be used in patients taking MAOIs or within 14 days of stopping such treatment.
Adrenal Insufficiency

Cases of adrenal insufficiency have been reported with opioid use, more often following greater than 1 month of use. Presentation of adrenal insufficiency may include non-specific symptoms and signs including nausea, vomiting, anorexia, fatigue, weakness, dizziness, and low blood pressure. If adrenal insufficiency is suspected, confirm the diagnosis with diagnostic testing as soon as possible. If adrenal insufficiency is diagnosed, treat with physiologic replacement doses of corticosteroids. Wean the patient off of the opioid to allow adrenal function to recover and continue corticosteroid treatment until adrenal function recovers. Other opioids may be tried as some cases reported use of a different opioid without recurrence of adrenal insufficiency. The information available does not identify any particular opioids as being more likely to be associated with adrenal insufficiency.
Severe Hypotension

Acetaminophen and codeine phosphate tablets may cause severe hypotension including orthostatic hypotension and syncope in ambulatory patients. There is increased risk in patients whose ability to maintain blood pressure has already been compromised by a reduced blood volume or concurrent administration of certain CNS depressant drugs (e.g., phenothiazines or general anesthetics) (see PRECAUTIONS; Drug Interactions). Regularly evaluate these patients for signs of hypotension after initiating or titrating the dosage of acetaminophen and codeine phosphate tablets. In patients with circulatory shock acetaminophen and codeine phosphate tablets may cause vasodilatation that can further reduce cardiac output and blood pressure. Avoid the use of acetaminophen and codeine phosphate tablets with circulatory shock.

Serious Skin Reactions

Rarely, acetaminophen may cause serious skin reactions such as acute generalized exanthematous pustulosis (AGEP), Stevens-Johnson Syndrome (SJS), and toxic epidermal necrolysis (TEN), which can be fatal. Patients should be informed about the signs of serious skin reactions, and use of the drug should be discontinued at the first appearance of skin rash or any other sign of hypersensitivity.
Risks of Use in Patients with Increased Intracranial Pressure, Brain Tumors, Head Injury, or Impaired Consciousness

In patients who may be susceptible to the intracranial effects of CO2retention (e.g., those with evidence of increased intracranial pressure or brain tumors), acetaminophen and codeine phosphate tablets may reduce respiratory drive, and the resultant CO2retention can further increase intracranial pressure. Monitor such patients for signs of sedation and respiratory depression, particularly when initiating therapy with acetaminophen and codeine phosphate tablets.

Opioids may also obscure the clinical course in a patient with a head injury. Avoid the use of acetaminophen and codeine phosphate tablets in patients with impaired consciousness or coma.
Hypersensitivity/Anaphylaxis

There have been post-marketing reports of hypersensitivity and anaphylaxis associated with the use of acetaminophen. Clinical signs included swelling of the face, mouth, and throat, respiratory distress, urticaria, rash, pruritus, and vomiting. There were infrequent reports of life-threatening anaphylaxis requiring emergency medical attention. Instruct patients to discontinue acetaminophen and codeine phosphate tablets immediately and seek medical care if they experience these symptoms. Do not prescribe acetaminophen and codeine phosphate tablets for patients with acetaminophen allergy (see PRECAUTIONS; Information for Patients/Caregivers).
Risks of Gastrointestinal Complications

Acetaminophen and codeine phosphate tablets are contraindicated in patients with known or suspected gastrointestinal obstruction, including paralytic ileus.

The Codeine in Acetaminophen and codeine phosphate tablets may cause spasm of the sphincter of Oddi. Opioids may cause increases in serum amylase. Regularly evaluate patients with biliary tract disease, including acute pancreatitis, for worsening symptoms.

Cases of opioid-induced esophageal dysfunction (OIED) have been reported in patients taking opioids. The risk of OIED may increase as the dose and/or duration of opioids increases. Regularly evaluate patients for signs and symptoms of OIED (e.g., dysphagia, regurgitation, non-cardiac chest pain), and, if necessary, adjust opioid therapy as clinically appropriate [see CLINICAL PHARMACOLOGY] .

Increased Risk of Seizures in Patients with Seizure Disorders

The codeine in acetaminophen and codeine phosphate tablets may increase the frequency of seizures in patients with seizure disorders, and may increase the risk of seizures occurring in other clinical settings associated with seizures. Regularly evaluate patients with a history of seizure disorders for worsened seizure control during acetaminophen and codeine phosphate tablets therapy.

Withdrawal

Do not rapidly reduce or abruptly discontinue acetaminophen and codeine phosphate tablets in a patient physically dependent on opioids. Rapid tapering of acetaminophen and codeine phosphate tablets in a patient physically dependent on opioids may lead to a withdrawal syndrome and return of pain [see DOSAGE AND ADMINISTRATION, DRUG ABUSE AND DEPENDENCE].

Additionally, avoid the use of mixed agonist/antagonist (e.g., pentazocine, nalbuphine, and butorphanol) or partial agonist (e.g., buprenorphine) analgesics in patients who are receiving a full opioid agonist analgesic, including acetaminophen and codeine phosphate tablets. In these patients, mixed agonist/antagonist and partial agonist analgesics may reduce the analgesic effect and/or may precipitate withdrawal symptoms [see PRECAUTIONS/ Drug Interactions].

Avoid the use of mixed agonist/antagonist (e.g, pentazocine, nalbuphine, and butorphanol) or partial agonist (e.g., buprenorphine) analgesics in patients who are receiving a full opioid agonist analgesic, including acetaminophen and codeine phosphate tablets. In these patients, mixed agonist/antagonist and partial analgesics may reduce the analgesic effect and/or precipitate withdrawal symptoms.

When discontinuing acetaminophen and codeine phosphate tablets, gradually taper the dosage (see DOSAGE AND ADMINISTRATION). Do not abruptly discontinue acetaminophen and codeine phosphate tablets (see DRUG ABUSE AND DEPENDENCE).

PRECAUTIONS

Risks of Driving and Operating Machinery

Acetaminophen and codeine phosphate tablets may impair the mental or physical abilities needed to perform potentially hazardous activities such as driving a car or operating machinery. Warn patients not to drive or operate dangerous machinery unless they are tolerant to the effects of acetaminophen and codeine phosphate tablets and know how they will react to the medication (see PRECAUTIONS; Information for Patients/Caregivers).

Information for Patients/Caregivers

Advise the patient to read the FDA-approved patient labeling (Medication Guide).

Storage and Disposal:
Because of the risks associated with accidental ingestion, misuse, and abuse, advise patients to store acetaminophen and codeine phosphate tablets securely, out of sight and reach of children, and in a location not accessible by others, including visitors to the home. Inform patients that leaving acetaminophen and codeine phosphate tablets unsecured can pose a deadly risk to others in the home. [See WARNINGS, DRUG ABUSE AND DEPENDENCE]

Advise patients and caregivers that when medicines are no longer needed, they should be disposed of promptly. Inform patients that medicine take-back options are the preferred way to safely dispose of most types of unneeded medicines. If no take back programs or DEA-registered collectors are available, instruct patients to dispose of acetaminophen and codeine phosphate tablets by following these four steps: • Mix acetaminophen and codeine phosphate tablets (do not crush) with an unpalatable substance such as dirt, cat litter, or used coffee grounds;
• Place the mixture in a container such as a sealed plastic bag;
• Throw the container in the household trash;
• Delete all personal information on the prescription label of the empty bottle
Inform patients that they can visit www.fda.gov/drugdisposal for additional information on disposal of unused medicines.

Addiction, Abuse and Misuse
Inform patients that the use of acetaminophen and codeine phosphate tablets, even when taken as recommended, can result in addiction, abuse, and misuse, which can lead to overdose and death (see WARNINGS). Instruct patients not to share acetaminophen and codeine phosphate tablets with others and to take steps to protect acetaminophen and codeine phosphate tablets from theft or misuse.
Life-Threatening Respiratory Depression
Inform patients of the risk of life-threatening respiratory depression, including information that the risk is greatest when starting acetaminophen and codeine phosphate tablets or when the dosage is increased, and that it can occur even at recommended dosages.

Educate patients and caregivers on how to recognize respiratory depression and emphasize the importance of calling 911 or getting emergency medical help right away in the event of a known or suspected overdose (see WARNINGS, Life Threatening Respiratory Depression).

Accidental Ingestion
Inform patients that accidental ingestion, especially by children, may result in respiratory depression or death (see WARNINGS). Instruct patients to take steps to store acetaminophen and codeine phosphate tablets securely. Advise patients to properly dispose of acetaminophen and codeine phosphate tablets in accordance with local state guidelines and/or regulations.

Interactions with Benzodiazepines and Other CNS Depressants
Inform patients and caregivers that potentially fatal additive effects may occur if acetaminophen and codeine phosphate tablets are used with benzodiazepines or other CNS depressants, including alcohol(e.g., non-benzodiazepine, sedative/hypnotics, anxiolytics, tranquilizers, muscle relaxants, general anesthetics, antipsychotics, gabapentinoids [gabapentin or pregabalin], and other opioids), and not to use these drugs concomitantly unless supervised by a healthcare provider (see WARNINGS, PRECAUTIONS; Drug Interactions).

Patient Access to an Opioid Overdose Reversal Agent for the Emergency Treatment of Opioid Overdose

Inform patients and caregivers about opioid overdose reversal agents (e.g., naloxone, nalmefene). Discuss the importance of having access to an opioid overdose reversal agent, especially if the patient has risk factors for overdose (e.g., concomitant use of CNS depressants, a history of opioid use disorder, or prior opioid overdose) or if there are household members (including children) or other close contacts at risk for accidental ingestion or opioid overdose.

Discuss with the patient the options for obtaining an opioid overdose reversal agent (e.g., prescription, over-the-counter, or as part of a community-based program) [see WARNINGS, DOSAGE AND ADMINISTRATION].

Educate patients and caregivers on how to recognize the signs and symptoms of an overdose.

Explain to patients and caregivers that effects of opioid overdose reversal agents like naloxone and nalmefeneare temporary, and that they must call 911 or get emergency medical help right away in all cases of known or suspected opioid overdose, even if an opioid overdose reversal agent is administered (see OVERDOSAGE).

Advise patients and caregivers:

how to treat with the overdose reversal agent in the event of an opioid overdose

• to tell family and friends about the opioid overdose reversal agent, and to keep it in a place where family and friends can access it in an emergency
• to read the Patient Information (or other educational material) that will come with their opioid overdose reversal agent. Emphasize the importance of doing this before an opioid emergency happens, so the patient and caregiver will know what to do.

Ultra-Rapid Metabolism of Codeine and Other Risk Factors for Life-Threatening Respiratory Depression in Children
Advise caregivers that acetaminophen and codeine phosphate tablets are contraindicated in all children younger than 12 years of age and in children younger than 18 years of age following tonsillectomy and/or adenoidectomy. Advise caregivers of children 12 to 18 years of age receiving acetaminophen and codeine phosphate tablets to monitor for signs of respiratory depression (see WARNINGS).

Hyperalgesia and Allodynia
Inform patients and caregivers not to increase opioid dosage without first consulting a clinician. Advise patients to seek medical attention if they experience symptoms of hyperalgesia, including worsening pain, increased sensitivity to pain, or new pain [see Warnings; Adverse Reactions].

Serotonin Syndrome
Inform patients that opioids could cause a rare but potentially life-threatening condition resulting from concomitant administration of serotonergic drugs. Warn patients of the symptoms and signs of serotonin syndrome and to seek medical attention right away if symptoms develop.

Instruct patients to inform their healthcare provider if they are taking, or plan to take serotonergic medications (see PRECAUTIONS; Drug Interactions).
MAOI Interaction
Inform patients not to take acetaminophen and codeine phosphate tablets while using any drugs that inhibit monoamine oxidase. Patients should not start MAOIs while taking acetaminophen and codeine phosphate tablets (see WARNINGS, Drug Interactions).

Important Administration Instructions
Instruct patients how to properly take acetaminophen and codeine phosphate tablets (see DOSAGE AND ADMINISTRATION).
• Advise patients not to adjust the dose of acetaminophen and codeine phosphate tablets without consulting a physician or other healthcare professional.
• If patients have been receiving treatment with acetaminophen and codeine phosphate tablets for more than a few weeks and cessation of therapy is indicated, counsel them on the importance of safely tapering the dose and that abruptly discontinuing the medication could precipitate withdrawal symptoms. Provide a dose schedule to accomplish a gradual discontinuation of the medication (see WARNINGS).
Important Discontinuation Instructions
In order to avoid developing withdrawal symptoms, instruct patients not to discontinue acetaminophen and codeine phosphate tablets without first discussing a tapering plan with the prescriber (see DOSAGE AND ADMINISTRATION)
Maximum Daily Dose of Acetaminophen
Inform patients not to take more than 4,000 milligrams of acetaminophen per day. Advise patients to call their healthcare provider if they have taken more than the recommended dose.
Driving or Operating Heavy Machinery
Inform patients that acetaminophen and codeine phosphate tablets may impair the mental and/or physical abilities required for the performance of potentially hazardous tasks such as driving a car or operating machinery and to avoid such tasks while taking this product, until they know how they will react to the medication.
Constipation
Advise patients of the potential for severe constipation, including management instructions and when to seek medical attention (see ADVERSE REACTIONS, CLINICAL PHARMACOLOGY).

Adrenal Insufficiency
Inform patients that opioids could cause adrenal insufficiency, a potentially life-threatening condition. Adrenal insufficiency may present with non-specific symptoms and signs such as nausea, vomiting, anorexia, fatigue, weakness, dizziness, and low blood pressure. Advise patients to seek medical attention if they experience a constellation of these symptoms (see WARNINGS).
Hypotension
Inform patients that acetaminophen and codeine phosphate tablets may cause orthostatic hypotension and syncope. Instruct patients how to recognize symptoms of low blood pressure and how to reduce the risk of serious consequences should hypotension occur (e.g., sit or lie down, carefully rise from a sitting or lying position) (see WARNINGS; Hypotension).

Anaphylaxis
Inform patients that anaphylaxis has been reported with ingredients contained in acetaminophen and codeine phosphate tablets. Advise patients how to recognize such a reaction, and if they develop signs of allergy such as a rash or difficulty breathing to stop taking acetaminophen and codeine phosphate tablets and seek medical attention. (see CONTRAINDICATIONS, ADVERSE REACTIONS).
Pregnancy
Neonatal Opioid Withdrawal Syndrome

Inform female patients of reproductive potential that use of acetaminophen and codeine phosphate tablets for an extended period of time during pregnancy can result in neonatal opioid withdrawal syndrome, which may be life-threatening if not recognized and treated (see WARNINGS, PRECAUTIONS: Pregnancy).

Embryo-Fetal Toxicity

Inform female patients of reproductive potential that acetaminophen and codeine phosphate tablets can cause fetal harm and to inform the prescriber of a known or suspected pregnancy (see PRECAUTIONS; Pregnancy).
Lactation
Advise women that breastfeeding is not recommended during treatment with acetaminophen and codeine phosphate tablets (see PRECAUTIONS; Nursing Mothers) .
Infertility
Inform patients that use of opioids for an extended period of time may cause reduced fertility. It is not known whether these effects on fertility are reversible [see Adverse Reaction].

Repackaged By / Distributed By: RemedyRepack Inc.

625 Kolter Drive, Indiana, PA 15701

(724) 465-8762

Drug Interactions

CYP2D6 Inhibitors

Codeine is metabolized by CYP2D6 to form morphine. The concomitant use of acetaminophen and codeine phosphate tablets and CYP2D6 inhibitors (e.g., paroxetine, fluoxetine, bupropion, quinidine) can increase the plasma concentration of codeine, but can decrease the plasma concentration of active metabolite morphine, which could result in reduced analgesic efficacy or symptoms of opioid withdrawal, particularly when an inhibitor is added after a stable dose of acetaminophen and codeine phosphate tablets is achieved (see CLINICAL PHARMACOLOGY).

After stopping a CYP2D6 inhibitor, as the effects of the inhibitor decline, the codeine plasma concentration will decrease but the active metabolite morphine plasma concentration will increase, which could increase or prolong adverse reactions and may cause potentially fatal respiratory depression (see CLINICAL PHARMACOLOGY).

If concomitant use with a CYP2D6 inhibitor is necessary, or if a CYP2D6 inhibitor is discontinued after concomitant use, consider dosage adjustment of acetaminophen and codeine phosphate tablets and evaluate patients closely at frequent intervals.

If concomitant use with CYP2D6 inhibitors is necessary, assess the patient for reduced efficacy or signs and symptoms of opioid withdrawal and consider increasing the dosage of acetaminophen and codeine phosphate tablets as needed.

After stopping use of a CYP2D6 inhibitor, consider reducing the dosage of acetaminophen and codeine phosphate tablets and evaluate the patient at frequent intervals for signs and symptoms of respiratory depression or sedation.

CYP3A4 Inhibitors
The concomitant use of acetaminophen and codeine phosphate tablets and CYP3A4 inhibitors, such as macrolide antibiotics (e.g., erythromycin), azole-antifungal agents (e.g. ketoconazole), and protease inhibitors(e.g., ritonavir), may result in an increase in codeine plasma concentrations , with subsequently greater metabolism by CYP2D6, resulting in greater morphine levels, which could increase or prolong adverse reactions and may cause potentially fatal respiratory depression, particularly when an inhibitor is added after a stable dose of acetaminophen and codeine phosphate tablets is achieved (see WARNINGS).

After stopping a CYP3A4 inhibitor, as the effects of the inhibitor decline, it may result in lower codeine levels, greater norcodeine levels, and less metabolism via CYP2D6 with resultant lower morphine levels (see CLINICAL PHARMACOLOGY), resulting in decreased opioid efficacy or a withdrawal syndrome in patients who had developed physical dependence to codeine.

If concomitant use of CYP3A4 inhibitor is necessary, consider dosage reduction of acetaminophen and codeine phosphate tablets until stable drug effects are achieved. Evaluate patients at frequent intervals for respiratory depression and sedation.

If a CYP3A4 inhibitor is discontinued, consider increasing the acetaminophen and codeine phosphate tablets dosage until stable drug effects are achieved. Evaluate for signs of opioid withdrawal.

CYP3A4 Inducers
The concomitant use of acetaminophen and codeine phosphate tablets and CYP3A4 inducers (e.g., rifampin, carbamazepine, phenytoin) can result in lower codeine levels, greater norcodeine levels, and less metabolism via CYP2D6 with resultant lower morphine levels (see CLINICAL PHARMACOLOGY),resulting in decreased efficacy or onset of a withdrawal syndrome in patients who have developed physical dependence (see WARNINGS).

After stopping a CYP3A4 inducer, as the effects of the inducer decline, codeine plasma concentrations may increase, with subsequently greater metabolism by cytochrome CYP2D6, resulting in greater morphine levels (see CLINICAL PHARMACOLOGY), which could increase or prolong both the therapeutic effects and adverse reactions, and may cause serious respiratory depression.

If concomitant use of a CYP3A4 inducer is necessary, evaluate the patient for reduced efficacy and signs of opioid withdrawal and consider increasing the acetaminophen and codeine phosphate tablets dosage as needed. Assess for respiratory depression and
Sedation.

If a CYP3A4 inducer is discontinued, consider a acetaminophen and codeine phosphate tablets dose reduction and evaluate patients at frequent intervals for signs of respiratory depression and sedation.

Benzodiazepines and Other Central Nervous System (CNS) Depressants
Due to additive pharmacologic effect, the concomitant use of benzodiazepines or other CNS depressants, including alcohol, other sedatives/hypnotics, anxiolytics, tranquilizers, muscle relaxants, general anesthetics, antipsychotics and other opioids, can increase the risk of hypotension, respiratory depression, profound sedation, coma, and death.

Reserve concomitant prescribing of these drugs for use in patients for whom alternative treatment options are inadequate. Limit dosages and durations to the minimum required. Inform patients and caregivers of this potential interaction, educate them on the signs and symptoms of respiratory depression (including sedation).If concomitant use is warranted, consider recommending or prescribing an opioid overdose reversal agent (see WARNINGS) Examples: Benzodiazepines and other sedatives/hypnotics, anxiolytics, tranquilizers, muscle relaxants, general anesthetics, antipsychotics, gabapentinoids (gabapentin or pregabalin), other opioids, alcohol.

Serotonergic Drugs
The concomitant use of opioids with other drugs that affect the serotonergic neurotransmitter system has resulted in serotonin syndrome. Examples of these drugs include, selective serotonin reuptake inhibitors (SSRIs), serotonin and norepinephrine reuptake inhibitors (SNRIs), tricyclic antidepressants (TCAs), triptans, 5-HT3 receptor antagonists, drugs that affect the serotonin neurotransmitter system (e.g., mirtazapine, trazodone, tramadol), certain muscle relaxants (i.e., cyclobenzaprine, metaxalone), and monoamine oxidase (MAO) inhibitors (used to treat psychiatric disorders and also others, such as linezolid and intravenous methylene blue) (see PRECAUTIONS; Information for Patients /Caregivers).

If concomitant use is warranted, frequently evaluate the patient, particularly during treatment initiation and dose adjustment. Discontinue acetaminophen and codeine phosphate tablets immediately if serotonin syndrome is suspected.

Monoamine Oxidase Inhibitors (MAOIs)
The concomitant use of opioids and MAOIs, such as phenelzine, tranylcypromine, linezolid, maymanifest as serotonin syndrome or opioid toxicity.
Advise patients taking acetaminophen and codeine phosphate tablets not to use MAOIs or within 14 days of stopping such treatment. If urgent use of an opioid is necessary, use test doses and frequent titration of small doses of other opioids (such as oxycodone, hydrocodone, oxymorphone, hydrocodone, or buprenorphine) to treat pain while closely monitoring blood pressure and signs and symptoms of CNS and respiratory depression.

Mixed Agonist/Antagonist and Partial Agonist Opioid Analgesics
The concomitant use of opioids with other opioid analgesics, such as butorphanol, nalbuphine, pentazocine, may reduce the analgesic effect of acetaminophen and codeine phosphate tablets and/or precipitate withdrawal symptoms.

Advise patient to avoid concomitant use of these drugs.

Muscle Relaxants
Codeine may enhance the neuromuscular blocking action of skeletal muscle relaxants and produce an increased degree of respiratory depression.

If concomitant use is warranted, because respiratory depression may be greater than otherwise expected, decrease the dosage of acetaminophen and codeine phosphate tablets and/or the muscle relaxant as necessary. Due to the risk of respiratory depression with concomitant use of skeletal muscle relaxants and opioids, consider recommending or prescribing an opioid overdose reversal agent (see WARNINGS).
Examples: cyclobenzaprine, metaxalone

Diuretics
Opioids can reduce the efficacy of diuretics by inducing the release of anti diuretic hormone.

If concomitant use is warranted, evaluate patients for signs of diminished diuresis and/or effects on blood pressure and increase the dosage of the diuretic as needed.

Anticholinergic Drugs
The concomitant use of anticholinergic drugs may increase risk of urinary retention and/or severe constipation, which may lead to paralytic ileus.
If concomitant use is warranted, evaluate patients for signs of urinary retention or reduced gastric motility when acetaminophen and codeine phosphate tablets are used concomitantly with anticholinergic drugs.

Drug/Laboratory Test Interactions

Codeine may increase serum amylase levels.

Acetaminophen may produce false-positive test results for urinary 5-hydroxyindoleacetic acid.

Carcinogenesis, Mutagenesis, Impairment of Fertility

Carcinogenesis

Long-term studies to evaluate the carcinogenic potential of the combination of codeine and acetaminophen have not been conducted

Two-year carcinogenicity studies have been conducted in F344/N rats and B6C3F1 mice. There was no evidence of carcinogenicity in male and female rats, respectively, at dietary doses up to 70 and 80mg/kg/day of codeine sulfate (approximately 2 times the maximum recommended daily dose of 360mg/day for adults on a mg/m2 basis) for two years. Similarly there was no evidence of carcinogenicity activity in male and female mice at dietary doses up to 400 mg/kg/day of codeine sulfate (approximately 5 times the maximum recommended daily dose of 360 mg/day for adults on a mg/m2 basis) for two years.

Long-term studies in mice and rats have been completed by the National Toxicology Program to evaluate the carcinogenic potential of acetaminophen. In 2-year feeding studies, F344/N rats and B6C3F1 mice were fed a diet containing acetaminophen up to 6000 ppm. Female rats demonstrated equivocal evidence of carcinogenic activity based on increased incidences of mononuclear cellleukemia at 0.8 times the maximum human daily dose (MHDD) of 4 grams/day, based on a body surface area comparison. In contrast, there was no evidence of carcinogenic activity in male rats that received up to 0.7 times or mice at up to 1.2–1.4 times the MHDD, based on a body surface area comparison.

Mutagenesis
Codeine sulfate was not mutagenic in the in vitrobacterial reverse mutation assay or clastogenic in the invitroChinese hamster ovary cell chromosome aberration assay.

In the published literature, acetaminophen has been reported to be clastogenic when administered at1500 mg/kg/day to the rat model (3.6-times the MHDD, based on a body surface area comparison). In contrast, no clastogenicity was noted at a dose of 750 mg/kg/day (1.8-times the MHDD, based on a body surface area comparison), suggesting a threshold effect.

Impairment of Fertility
No nonclinical fertility studies have been conducted with codeine or the combination of codeine and acetaminophen.

In studies conducted by the National Toxicology Program, fertility assessments with acetaminophen have been completed in Swiss CD-1 mice via a continuous breeding study. There were no effects on fertility parameters in mice consuming up to 1.7 times the MHDD of acetaminophen, based on a body surface area comparison. Although there was no effect on sperm motility or sperm density in the epididym is, there was a significant increase in the percentage of abnormal sperm in mice consuming1.78 times the MHDD (based on a body surface comparison) and there was a reduction in the number of mating pairs producing a fifth litter at this dose, suggesting the potential for cumulative toxicity with chronic administration of acetaminophen near the upper limit of daily dosing.

Published studies in rodents report that oral acetaminophen treatment of male animals at doses that are1.2 times the MHDD and greater (based on a body surface comparison) result in decreased testicular weights, reduced spermatogenesis, reduced fertility, and reduced implantation sites in females given the same doses. These effects appear to increase with the duration of treatment. The clinical significance of these findings is not known.

Infertility

Use of opioids for an extended period of time may cause reduced fertility in females and males of reproductive potential. It is not known whether these effects on fertility are reversible (see ADVERSE REACTIONS).

Pregnancy

Teratogenic Effects

Codeine
A study in rats and rabbits reported no teratogenic effect of codeine administered during the period of organogenesis in doses ranging from 5 to 120 mg/kg. In the rat, doses at the 120 mg/kg level, in the toxic range for the adult animal, were associated with an increase in embryo resorption at the time of implantation. In another study a single 100 mg/kg subcutaneous dose of codeine administered to pregnant mice reportedly resulted in delayed ossification in the offspring.

Nonteratogenic Effects

Fetal/Neonatal Adverse Reactions

Use of opioid analgesics for an extended period of time during pregnancy for medical or nonmedical purposes can result in physical dependence in the neonate and neonatal opioid withdrawal syndrome shortly after birth.

Neonatal opioid withdrawal syndrome presents as irritability, hyperactivity and abnormal sleep pattern, high pitched cry, tremor, vomiting, diarrhea and failure to gain weight. The onset, duration, and severity of neonatal opioid withdrawal syndrome vary based on the specific opioid used, duration of use, timing and amount of last maternal use, and rate of elimination of the drug by the newborn. Observe newborns for symptoms of neonatal opioid withdrawal syndrome and manage accordingly (see WARNINGS).

Labor or Delivery

Opioids cross the placenta and may produce respiratory depression and psycho-physiologic effects in neonates. An opioid overdose reversal agent, such as naloxone or nalmefene, must be available for reversal of opioid-induced respiratory depression in the neonate. Acetaminophen and codeine phosphate tablets are not recommended for use in pregnant women during or immediately prior to labor, when other analgesic techniques are more appropriate. Opioid analgesics, including acetaminophen and codeine phosphate tablets, and can prolong labor through actions which temporarily reduce the strength, duration, and frequency of uterine contractions. However, this effect is not consistent and may be offset by an increased rate of cervical dilation, which tends to shorten labor. Monitor neonates exposed to opioid analgesics during labor for signs of excess sedation and respiratory depression.

Narcotic analgesics should be avoided during labor if delivery of a premature infant is anticipated. If the mother has received narcotic analgesics during labor, newborn infants should be observed closely for signs of respiratory depression. Resuscitation may be required (see OVERDOSAGE). The effect of codeine, if any, on the later growth, development, and functional maturation of the child is unknown.

Nursing Mothers

Codeine and its active metabolite, morphine, are present in human milk. There are published studies and cases that have reported excessive sedation, respiratory depression, and death in infants exposed to codeine via breast milk. Women who are ultra-rapid metabolizers of codeine achieve higher than expected serum levels of morphine, potentially leading to higher levels of morphine in breast milk that can be dangerous in their breastfed infants. In women with normal codeine metabolism (normal CYP2D6 activity), the amount of codeine secreted into human milk is low and dose-dependent.
There is no information on the effects of codeine on milk production. Because of the potential for serious adverse reactions, including excess sedation, respiratory depression, and death in a breastfed infant, advise patients that breastfeeding is not recommended during treatment with acetaminophen and codeine phosphate tablets (see WARNINGS).

Acetaminophen is excreted in breast milk in small amounts, but the significance of its effect on nursing infants is not known. Because of the potential for serious adverse reactions in nursing infants from acetaminophen, a decision should be made whether to discontinue nursing or discontinue the drug, taking into account the importance of the drug to the mother.

Clinical Considerations
If infants are exposed to acetaminophen and codeine phosphate tablets through breast milk, they should be monitored for excess sedation and respiratory depression. Withdrawal symptoms can occur in breastfed infants when maternal administration of an opioid analgesic is stopped, or when breastfeeding is stopped.

Pediatric Use

The safety and effectiveness of acetaminophen and codeine phosphate tablets with Codeine in pediatric patients below the age of 18have not been established.
Life-threatening respiratory depression and death have occurred in children who received codeine (see WARNINGS). In most of the reported cases, these events followed tonsillectomy and/or adenoidectomy, and many of the children had evidence of being ultra-rapid metabolizers of codeine (i.e., multiple copies of the gene for CYP2D6 or high morphine concentrations). Children with sleep apnea may be particularly sensitive to the respiratory depressant effects of codeine.

Because of the risk of life-threatening respiratory depression and death:
• Acetaminophen and codeine phosphate tablets are contraindicated for all children younger than 12 years of age (see CONTRAINDICATIONS).
• Acetaminophen and codeine phosphate tablets are contraindicated for post-operative management in pediatric patients younger than 18 years of age following tonsillectomy and/or adenoidectomy (see CONTRAINDICATIONS).
• Avoid the use of acetaminophen and codeine phosphate tablets in adolescents 12 to 18 years of age who have other risk factors that may increase their sensitivity to the respiratory depressant effects of codeine unless the benefits outweigh the risks. Risk factors include conditions associated with hypoventilation, such as post-operative status, obstructive sleep apnea, obesity, severe pulmonary disease, neuromuscular disease, and concomitant use of other medications that cause respiratory depression (see WARNINGS).

Geriatric Use

Elderly patients (aged 65 years or older) may have increased sensitivity to acetaminophen and codeine phosphate tablets. In general, use caution when selecting a dosage for an elderly patient, usually starting at the low end of the dosing range, reflecting the greater frequency of decreased hepatic, renal, or cardiac function and of concomitant disease or other drug therapy.

Respiratory depression is the chief risk for elderly patients treated with opioids, and has occurred after large initial doses were administered to patients who were not opioid-tolerant or when opioids were co-administered with other agents that depress respiration. Titrate the dosage of acetaminophen and codeine phosphate tablets slowly in geriatric patients and frequently reevaluate the patient for signs of central nervous system depression (see WARNINGS).

These drugs are known to be substantially excreted by the kidney, and the risk of adverse reactions to this drug may be greater in patients with impaired renal function. Because elderly patients are more likely to have decreased renal function, care should be taken in dose selection, and it may be useful to regularly evaluate renal function.

ADVERSE REACTIONS

The following serious adverse reactions are described, or described in greater detail, in other sections:
• Addiction, Abuse, and Misuse (see WARNINGS)
• Life-Threatening Respiratory Depression (see WARNINGS)
• Ultra-Rapid Metabolism of Codeine and Other Risk Factors for Life-Threatening Respiratory Depression in Children (see WARNINGS)
• Neonatal Opioid Withdrawal Syndrome (see WARNINGS)
• Interactions with CNS Depressants (see WARNINGS)
• Severe Hypotension (see WARNINGS)
• Gastrointestinal Adverse Reactions (see WARNINGS)
• Seizures (see WARNINGS)
• Withdrawal (see WARNINGS)
• Opioid-Induced Hyperalgesia and Allodynia (See WARNINGS)

The following adverse reactions have been identified during post-approval use of acetaminophen and codeine phosphate tablets. Because some of these reactions were reported voluntarily from a population of uncertain size, it is not always possible to reliably estimate their frequency or establish a causal relationship to drug exposure.

Serious adverse reactions associated with codeine are respiratory depression and, to a lesser degree, circulatory depression, respiratory arrest, shock, and cardiac arrest.

The most frequently observed adverse reactions with codeine administration include drowsiness, lightheadedness, dizziness, sedation, shortness of breath, nausea, vomiting, sweating, and constipation.

Other adverse reactions include allergic reactions, euphoria, dysphoria, abdominal pain, pruritus, rash, thrombocytopenia, and agranulocytosis.

Other less frequently observed adverse reactions expected from opioid analgesics, including acetaminophen and codeine phosphate tablets:

Cardiovascular system: faintness, flushing, hypotension, palpitations, syncope.

Digestive System: abdominal cramps, anorexia, diarrhea, dry mouth, gastrointestinal distress, pancreatitis.

Nervous system: anxiety, drowsiness, fatigue, headache, insomnia, nervousness, shakiness, somnolence, vertigo, visual disturbances, weakness.

Skin and Appendages: fixed eruption, rash, sweating, urticarial.
• Serotonin syndrome:Cases of serotonin syndrome, a potentially life-threatening condition, havebeen reported during concomitant use of opioids with serotonergic drugs.
• Adrenal insufficiency:Cases of adrenal insufficiency have been reported with opioid use, moreoften following greater than one month of use.
• Anaphylaxis:Anaphylaxis has been reported with ingredients contained in acetaminophen and codeine phosphate tablets.
• Androgen deficiency:Cases of androgen deficiency have occurred with use of opioids for an extended period of time (see CLINICAL PHARMACOLOGY).
• Hyperalgesia and Allodynia:Cases of hyperalgesia and allodynia have been reported with opioid therapy of any duration [see Warnings].
• Hypoglycemia:Cases of hypoglycemia have been reported in patients taking opioids. Most reports were in patients with at least one predisposing risk factor (e.g., diabetes).

Opioid-induced esophageal dysfunction (OIED): Cases of OIED have been reported in patients taking opioids, and may occur more frequently in patients taking higher doses of opioids, and/or in patients taking opioids longer term [see WARNINGS].

Adverse Reactions from Observational Studies
A prospective, observational cohort study estimated the risks of addiction, abuse, and misuse in patients initiating long-term use of Schedule II opioid analgesics between 2017 and 2021. Study participants included in one or more analyses had been enrolled in selected insurance plans or health systems for at least one year, were free of at least one outcome at baseline, completed a minimum number of follow-up assessments, and either: 1) filled multiple extended-release/long-acting opioid analgesic prescriptions during a 90 day period (n=978); or 2) filled any Schedule II opioid analgesic prescriptions covering at least 70 of 90 days (n=1,244). Those included also had no dispensing of the qualifying opioids in the previous 6 months.

Over 12 months:
• approximately 1% to 6% of participants across the two cohorts newly met criteria for addiction, as assessed with two validated interview-based measures of moderate-to-severe opioid use disorder based on Diagnostic and Statistical Manual of Mental Disorders, Fifth Edition (DSM-5) criteria, and
• approximately 9% and 22% of participants across the two cohorts newly met criteria for prescription opioid abuse and misuse [defined in DRUG ABUSE AND DEPENDENCE], respectively, as measured with a validated self-reported instrument.

A retrospective, observational cohort study estimated the risk of opioid-involved overdose or opioid overdose-related death in patients with new long-term use of Schedule II opioid analgesics from 2006 through 2016 (n=220,249). Included patients had been enrolled in either one of two commercial insurance programs, one managed care program, or one Medicaid program for at least 9 months. New long-term use was defined as having Schedule II opioid analgesic prescriptions covering at least 70 days’ supply over the 3 months prior to study entry and none during the preceding 6 months. Patients were excluded if they had an opioid-involved overdose in the 9 months prior to study entry. Overdose was measured using a validated medical code-based algorithm with linkage to the National Death Index database. The 5-year cumulative incidence estimates for opioid-involved overdose or opioid overdose-related death ranged from approximately 1.5% to 4% across study sites, counting only the first event during follow-up. Approximately 17% of first opioid overdoses observed over the entire study period (5-11 years, depending on the study site) were fatal. Higher baseline opioid dose was the strongest and most consistent predictor of opioid-involved overdose or opioid overdose-related death. Study exclusion criteria may have selected patients at lower risk of overdose, and substantial loss to follow-up (approximately 80%) also may have biased estimates.

The risk estimates from the studies described above may not be generalizable to all patients receiving opioid analgesics, such as those with exposures shorter or longer than the duration evaluated in the studies.

DRUG ABUSE AND DEPENDENCE

Controlled Substance

Acetaminophen and codeine phosphate tablets contain codeine. Codeine in combination with acetaminophen, is a Schedule III controlled substance.

Abuse

Acetaminophen and Codeine Phosphate Tablets contains acetaminophen and codeine phosphate, a substance with high potential for misuse and abuse, which can lead to the development of substance used is order, including addiction [see Warnings].

Misuse is the intentional use, for therapeutic purposes, of a drug by an individual in a way other than prescribed by a healthcare provider or for whom it was not prescribed.

Abuse is the intentional, non-therapeutic use of a drug, even once, for its desirable psychological or physiological effects.

Drug addiction is a cluster of behavioral, cognitive, and physiological phenomena that may include a strong desire to take the drug, difficulties in controlling drug use (e.g., continuing drug use despite harmful consequences, giving a higher priority to drug use than other activities and obligations), and possible tolerance or physical dependence.

Misuse and abuse of acetaminophen and codeine phosphate tablets increases risk of overdose, which may lead to central nervous system and respiratory depression, hypotension, seizures, and death. The risk is increased with concurrent abuse of acetaminophen and codeine phosphate tablets with alcohol and other CNS depressants. Abuse of and addiction to opioids in some individuals may not be accompanied by concurrent tolerance and symptoms of physical dependence. In addition, abuse of opioids can occur in the absence of addiction.

All patients treated with opioids require careful and frequent reevaluation for signs of misuse, abuse, and addiction, because use of opioid analgesic products carries the risk of addiction even under appropriate medical use. Patients at high risk of acetaminophen and codeine phosphate tablets abuse include those with a history of prolonged use of any opioid, including products containing oxycodone, those with a history of drug or alcohol abuse, or those who use acetaminophen and codeine phosphate tablets in combination with other abused drugs.

“Drug-seeking” behavior is very common in persons with substance use disorders. Drug-seeking tactics include emergency calls or visits near the end of office hours, refusal to undergo appropriate examination, testing, or referral, repeated “loss” of prescriptions, tampering with prescriptions, and reluctance to provide prior medical records or contact information for other treating healthcare provider(s). “Doctor shopping” (visiting multiple prescribers to obtain additional prescriptions) is common among people who abuse drugs and people with substance use disorder. Preoccupation with achieving adequate pain relief can be appropriate behavior in a patient with inadequate pain control.

Acetaminophen and codeine phosphate tablets, like other opioids, can be diverted for nonmedical use into illicit channels of distribution. Careful record-keeping of prescribing information, including quantity, frequency, and renewal requests, as required by state and federal law, is strongly advised.

Proper assessment of the patient, proper prescribing practices, periodic reevaluation of therapy, and proper dispensing and storage are appropriate measures that help to limit abuse of opioid drugs.

Risks Specific to Abuse of Acetaminophen and Codeine Phosphate Tablets
Abuse of acetaminophen and codeine phosphate tablets poses a risk of overdose and death. The risk is increased with concurrent use of acetaminophen and codeine phosphate tablets with alcohol and/or other CNS depressants.

Parenteral drug abuse is commonly associated with transmission of infectious diseases such as hepatitis and HIV.

Dependence

Both tolerance and physical dependence can develop during use of opioid therapy.
Tolerance is a physiological state characterized by a reduced response to a drug after repeated administration (i.e., a higher dose of a drug is required to produce the same effect that was once obtained at a lower dose).

Physical dependence is a state that develops as a result of a physiological adaptation in response to repeated drug use, manifested by withdrawal signs and symptoms after abrupt discontinuation or a significant dose reduction of a drug. Withdrawal may be precipitated through the administration of drugs with opioid antagonist activity (e.g., naloxone, nalmefene), mixed agonist/antagonist analgesics (e.g.,pentazocine, butorphanol, nalbuphine), or partial agonists (e.g., buprenorphine). Physical dependence may not occur to a clinically significant degree until after several days to weeks of continued opioid usage.

Do not rapidly reduce or abruptly discontinue acetaminophen and codeine phosphate tablets in a patient physically dependent on opioids. Rapid tapering of acetaminophen and codeine phosphate tablets in a patient physically dependent on opioids may lead to serious withdrawal symptoms, uncontrolled pain, and suicide. Rapid discontinuation has also been associated with attempts to find other sources of opioid analgesics, which may be confused with drug-seeking for abuse.

When discontinuing acetaminophen and codeine phosphate tablets, gradually taper the dosage using a patient-specific plan that considers the following: the dose of acetaminophen and codeine phosphate tablets the patient has been taking, the duration of treatment, and the physical and psychological attributes of the patient. To improve the likelihood of a successful taper and minimize withdrawal symptoms, it is important that the opioid tapering schedule is agreed upon by the patient. In patients taking opioids for an extended period of time at high doses, ensure that a multimodal approach to pain management, including mental health support (if needed), is in place prior to initiating an opioid analgesic taper [see DOSAGE AND ADMINISTRATION, WARNINGS].

Infants born to mothers physically dependent on opioids will also be physically dependent and may exhibit respiratory difficulties and withdrawal signs (see Pregnancy).

OVERDOSAGE

Following an acute overdosage, toxicity may result from codeine or acetaminophen.
Clinical Presentation

Codeine
Acute overdose with codeine phosphate can be manifested by respiratory depression, somnolence progressing to stupor or coma, skeletal muscle flaccidity, cold and clammy skin, constricted pupils, and, in some cases, pulmonary edema, bradycardia, hypotension, hypoglycemia, partial or complete airway obstruction, atypical snoring, and death. Marked mydriasis rather than miosis may be seen with hypoxia in overdose situations. [ see CLINICAL PHARMACOLOGY] . Toxic leukoencephalopathy has been reported after opioid overdose and can present hours, days, or weeks after apparent recovery from the initial intoxication.
Acetaminophen
Dose-dependent, potentially fatal hepatic necrosis is the most serious adverse effect of acetaminophen overdose. Renal tubular necrosis, hypoglycemic coma, and coagulation defects may also occur.

Early symptoms following a potentially hepatotoxic overdose may include; anorexia, nausea, vomiting, diaphoresis, pallor and general malaise. Clinical and laboratory evidence of hepatic toxicity may not be apparent until 48 to 72 hours post-ingestion.
Treatment of Overdose

Codeine
In case of overdose, priorities are the reestablishment of a patent and protected airway and institution of assisted or controlled ventilation, if needed. Employ other supportive measures (including oxygen and vasopressors) in the management of circulatory shock and pulmonary edema as indicated. Cardiac arrest or arrhythmias will require advanced life-support measures.
For clinically significant respiratory or circulatory depression secondary to acetaminophen and codeine phosphate tablets overdose, administer an opioid overdose reversal agent such as naloxone or nalmefene.
Because the duration of opioid reversal is expected to be less than the duration of action of codeine in acetaminophen and codeine phosphate tablets, carefully monitor the patient until spontaneous respiration is reliably reestablished. If the response to an opioid overdose reversal agent is suboptimal or only brief in nature, administer additional reversal agent as directed by the product's prescribing information.
In an individual physically dependent on opioids, administration of the recommended usual dosage of the opioid overdose reversal agent will precipitate an acute withdrawal syndrome. The severity of the withdrawal symptoms experienced will depend on the degree of physical dependence and the dose of the reversal agent administered. If a decision is made to treat serious respiratory depression in the physically dependent patient, administration of the reversal agent should be begun with care and by titration with smaller than usual doses of the reversal agent.
Acetaminophen
Gastric decontamination with activated charcoal should be administered just prior to N-acetylcysteine (NAC) to decrease systemic absorption if acetaminophen ingestion is known or suspected to have occurred within a few hours of presentation. Serum acetaminophen levels should be obtained immediately if the patient presents 4 hours or more after ingestion to assess potential risk of hepatotoxicity; acetaminophen levels drawn less than 4 hours post-ingestion may be misleading. To obtain the best possible outcome, (NAC) should be administered as soon as possible where impending or evolving liver injury is suspected .Intravenous NAC may be administered when circumstances preclude oral administration.
Vigorous supportive therapy is required in severe intoxication. Procedures to limit the continuing absorption of the drug must be readily performed since the hepatic injury is dose-dependent and occurs early in the course of intoxication.

DOSAGE AND ADMINISTRATION

Important Dosage and Administration Instructions

Acetaminophen and codeine phosphate tablets should be prescribed only by healthcare professionals who are knowledgeable about the use of opioids and how to mitigate the associated risks.

Use the lowest effective dosage for the shortest duration of time consistent with individual patient treatment goals [see Warnings]. Because the risk of overdose increases as opioid doses increase, reserve titration to higher doses of acetaminophen and codeine phosphate tablets for patients in whom lower doses are insufficiently effective and in whom the expected benefits of using a higher dose opioid clearly outweigh the substantial risks.

Many acute pain conditions (e.g., the pain that occurs with a number of surgical procedures or acute musculoskeletal injuries) require no more than a few days of an opioid analgesic. Clinical guidelines on opioid prescribing for some acute pain conditions are available.

There is variability in the opioid analgesic dose and duration needed to adequately manage pain due both to the cause of pain and to individual patient factors. Initiate the dosing regimen for each patient individually, taking into account the patient’s underlying cause and severity of pain, prior analgesic treatment and response, and risk factors for addiction, abuse, and misuse [see Warnings].

Respiratory depression can occur at any time during opioid therapy, especially when initiating and following dosage increases with acetaminophen and codeine phosphate tablets. Consider this risk when selecting an initial dose and when making dose adjustments [see Warnings].

Patient Access to an Opioid Overdose Reversal Agent for the Emergency Treatment of Opioid Overdose

Inform patients and caregivers about opioid overdose reversal agents (e.g., naloxone, nalmefene). Discuss the importance of having access to an opioid overdose reversal agent, especially if the patient has risk factors for overdose (e.g., concomitant use of CNS depressants, a history of opioid use disorder, or prior opioid overdose) or if there are household members (including children) or other close contacts at risk for accidental ingestion or opioid overdose. The presence of risk factors for overdose should not prevent the management of pain in any patient [see WARNINGS; Addiction, Abuse, and Misuse; Life-Threatening Respiratory Depression; Risks from Concomitant Use with Benzodiazepines or Other CNS Depressants].

Discuss the options for obtaining an opioid overdose reversal agent (e.g., prescription, over-the-counter, or as part of a community-based program).
There are important differences among the opioid overdose reversal agents, such as route of administration, product strength, approved patient age range, and pharmacokinetics. Be familiar with these differences, as outlined in the approved labeling for those products, prior to recommending or prescribing such an agent.

Initial Dosage
Use of Acetaminophen and Codeine Phosphate Tablets as the First Opioid Analgesic
Initiate treatment with acetaminophen and codeine phosphate tablets in a dosing range of 300 mg to 600 mg of acetaminophen and 30 mg to 60 mg of codeine phosphate every 4 hours as needed for pain, at the lowest dose necessary to achieve adequate analgesia. Titrate the dose based upon the individual patient’s response to their initial dose of acetaminophen and codeine phosphate tablets.
The usual adult dosage is:
Acetaminophen and codeine phosphate tablets (codeine 15 mg and acetaminophen 300 mg): Take 1 to 2 tablets every 4 hours as needed for pain.
Acetaminophen and codeine phosphate tablets (codeine 30 mg and acetaminophen 300 mg): Take 1 to 2 tablets every 4 hours as needed for pain.
Acetaminophen and codeine phosphate tablets (codeine 60 mg and acetaminophen 300 mg): Take one tablet every 4 hours as needed for pain.

 | Single Doses (Range) | Maximum 24-Hour Dose
Codeine Phosphate | 15 mg to 60 mg | 360 mg
Acetaminophen | 300 mg to 1,000 mg | 4,000 mg

The prescriber must determine the number of tablets per dose, and the maximum number of tablets per24 hours, based upon the above dosage guidance. This information should be conveyed in the prescription.

Conversion from Other Opioids to acetaminophen and codeine phosphate tablets
There is inter-patient variability in the potency of opioid drugs and opioid formulations. Therefore, a conservative approach is advised when determining the total daily dosage of acetaminophen and codeine phosphate tablets. It is safer to underestimate a patient's 24-hour acetaminophen and codeine phosphate tablets dosage than to overestimate the 24-hour acetaminophen and codeine phosphate tablets dosage and manage an adverse reaction due to overdose.
Titration and Maintenance of Therapy

Individually titrate acetaminophen and codeine phosphate tablets to a dose that provides adequate analgesia and minimizes adverse reactions. Continually reevaluate patients receiving acetaminophen and codeine phosphate tablets to assess the maintenance of pain control, signs and symptoms of opioid withdrawal, and other adverse reactions, as well as reassess for the development of addiction, abuse, or misuse (see WARNINGS). Frequent communication is important among the prescriber, other members of the healthcare team, the patient, and the caregiver/family during periods of changing analgesic requirements, including initial titration.

If the level of pain increases after dosage stabilization, attempt to identify the source of increased pain before increasing the acetaminophen and codeine phosphate tablets dosage. If after increasing the dosage, unacceptable opioid-related adverse reactions are observed (including an increase in pain after dosage increase), consider reducing the dosage (see WARNINGS). Adjust the dosage to obtain an appropriate balance between management of pain and opioid-related adverse reactions.

Safe Reduction and Discontinuation of Codeine Phosphate
Do not rapidly reduce or abruptly discontinue codeine phosphate in patients who may be physically dependent on opioids. Rapid reduction or abrupt discontinuation of opioid analgesics in patients who are physically dependent on opioids has resulted in serious withdrawal symptoms, uncontrolled pain, and suicide. Rapid reduction or abrupt discontinuation has also been associated with attempts to find other sources of opioid analgesics, which may be confused with drug-seeking for abuse. Patients may also attempt to treat their pain or withdrawal symptoms with illicit opioids, such as heroin, and other substances.

When a decision has been made to decrease the dose or discontinue therapy in an opioid-dependent patient taking acetaminophen and codeine phosphate tablets, there are a variety of factors that should be considered, including the total daily dose of opioid (including acetaminophen and codeine phosphate tablets) the patient has been taking, the duration of treatment, the type of pain being treated, and the physical and psychological attributes of the patient. It is important to ensure ongoing care of the patient and to agree on an appropriate tapering schedule and follow-up plan so that patient and provider goals and expectations are clear and realistic. When opioid analgesics are being discontinued due to a suspected substance use disorder, evaluate and treat the patient, or refer for evaluation and treatment of the substance use disorder. Treatment should include evidence-based approaches, such as medication assisted treatment of opioid use disorder. Complex patients with co-morbid pain and substance use disorders may benefit from referral to a specialist.

There are no standard opioid tapering schedules that are suitable for all patients. Good clinical practice dictates a patient-specific plan to taper the dose of the opioid gradually. For patients on acetaminophen and codeine phosphate tablets who are physically opioid-dependent, initiate the taper by a small enough increment (e.g., no greater than 10% to 25% of the total daily dose) to avoid withdrawal symptoms, and proceed with dose-lowering at an interval of every 2 to 4 weeks. Patients who have been taking opioids for briefer periods of time may tolerate a more rapid taper.

It may be necessary to provide the patient with lower dosage strengths to accomplish a successful taper. Reassess the patient frequently to manage pain and withdrawal symptoms, should they emerge. Common withdrawal symptoms include restlessness, lacrimation, rhinorrhea, yawning, perspiration, chills, myalgia, and mydriasis. Other signs and symptoms also may develop, including irritability, anxiety, backache, joint pain, weakness, abdominal cramps, insomnia, nausea, anorexia, vomiting, diarrhea, or increased blood pressure, respiratory rate, or heart rate. If withdrawal symptoms arise, it may be necessary to pause the taper for a period of time or raise the dose of the opioid analgesic to the previous dose, and then proceed with a slower taper. In addition, evaluate patients for any changes in mood, emergence of suicidal thoughts, or use of other substances.

When managing patients taking opioid analgesics, particularly those who have been treated for an extended period of time, and/or with high doses for chronic pain, ensure that a multimodal approach to pain management, including mental health support (if needed), is in place prior to initiating an opioid analgesic taper. A multimodal approach to pain management may optimize the treatment of chronic pain, as well as assist with the successful tapering of the opioid analgesic [see WARNINGS; Withdrawal, DRUG ABUSE AND DEPENDENCE].

HOW SUPPLIED

Acetaminophen and Codeine Phosphate Tablets USP, 300 mg/60 mg contain acetaminophen 300 mg and codeine phosphate 60 mg. The tablets are blue colored, round flat-faced beveled edge, debossed one side with W243.

NDC: 70518-2764-00

NDC: 70518-2764-01

PACKAGING: 30 in 1 BLISTER PACK

PACKAGING: 30 in 1 BLISTER PACK

Store Acetaminophen and Codeine Phosphate Tablets, USP at 20° to 25°C (68° to 77°F). [See USP Controlled Room Temperature.]

Dispense in tight, light-resistant container as defined in the USP.

Store acetaminophen and codeine phosphate tablets securely and dispose of properly (see PRECAUTIONS, Information for Patients).

Repackaged and Distributed By:

Remedy Repack, Inc.

625 Kolter Dr. Suite #4 Indiana, PA 1-724-465-8762

Medication Guide

Acetaminophen and Codeine Phosphate Tablets USP, CIII
(a seet' a min' oh fen and koe' deen fos' fate)

Acetaminophen and codeine phosphate tablets are:
· A strong prescription pain medicine that contains an opioid (narcotic) that is used to manage mild to moderate pain, when other pain treatments such as non-opioid pain medicines do not treat your pain well enough or you cannot tolerate them.
· An opioid pain medicine that can put you at risk for overdose and death. Even if you take your dose correctly as prescribed you are at risk for opioid addiction, abuse, and misuse that can lead to death.

Important information about acetaminophen and codeine phosphate tablets:
· Get emergency help or call 911 right away if you take too much acetaminophen and codeine phosphate tablets (overdose).When you first start taking acetaminophen and codeine phosphate tablets, when your dose is changed, or if you take too much (overdose), serious or life-threatening breathing problems that can lead to death may occur. Talk to your healthcare provider about naloxone, a medicine for the emergency treatment of an opioid overdose.
· Taking acetaminophen and codeine phosphate tablets with other opioid medicines, benzodiazepines, gabapentinoids (gabapentin or pregabalin), alcohol, or other central nervous system depressants (including street drugs) can cause severe drowsiness, decreased awareness, breathing problems, coma and death.
· Never give anyone else your acetaminophen and codeine phosphate tablets. They could die from taking it. Selling or giving away acetaminophen and codeine phosphate tablets is against the law.
· Store acetaminophen and codeine phosphate tablets securely, out of sight and reach of children, and in a location not accessible by others, including visitors to the home.

Important Information Guiding Use in Pediatric Patients
· Do not give acetaminophen and codeine phosphate tablets to a child younger than 12 years of age.
· Do not give acetaminophen and codeine phosphate tablets to a child younger than 18 years of age after surgery to remove the tonsils and/or adenoids.
· Avoid giving acetaminophen and codeine phosphate tablets to children between 12 to 18 years of age who have risk factors for breathing problems such as obstructive sleep apnea, obesity, or underlying lung problems.
Do not take acetaminophen and codeine phosphate tablets if you have:
· severe asthma, trouble breathing, or other lung problems.
· a bowel blockage or narrowing of the stomach or intestines.
· previously had an allergic reaction to codeine or acetaminophen.

Before taking acetaminophen and codeine phosphate tablets, tell your healthcare provider if you have a history of:
· head injury, seizures
· liver, kidney, thyroid problems
· problems urinating
· pancreas or gallbladder problems
· abuse of street or prescription drugs, alcohol addiction, opioid overdose, or mental health problems
· have been told by your healthcare provider that you are a "rapid metabolizer" of certain medicines.
Tell your healthcare provider if you are:
· Noticing your pain getting worse. If your pain gets worse after you take acetaminophen and codeine phosphate tablets, do not take more of acetaminophen and codeine phosphate tablets without first talking to your healthcare provider. Talk to your healthcare provider if the pain that you have increases, if you feel more sensitive to pain, or if you have new pain after taking acetaminophen and codeine phosphate tablets.
· Pregnant or planning to become pregnant.Use of acetaminophen and codeine phosphate tablets for an extended period of time during pregnancy can cause withdrawal symptoms in your newborn baby that could be life-threatening if not recognized and treated.
· Breastfeeding.Not recommended; may harm your baby.
· Livingin a household where there are small children or someone who has abused street or prescription drugs.
· Taking prescription or over-the-counter medicines, vitamins, or herbal supplements. Taking acetaminophen and codeine phosphate tablets with certain other medicines can cause serious side effects that could lead to death.

When taking acetaminophen and codeine phosphate tablets:
· Do not change your dose. Take acetaminophen and codeine phosphate tablets exactly as prescribed by your healthcare provider. Use the lowest dose possible for the shortest time needed.
· For acute (short-term) pain, you may only need to take acetaminophen and codeine phosphate tablets for a few days. You may have some acetaminophen and codeine phosphate tablets left over that you did not use. See disposal information at the bottom of this section for directions on how to safely throw away (dispose of) your unused acetaminophen and codeine phosphate tablets.
· Take your prescribed dose every 4 hours at the same time everyday as needed for pain. Do not take more than your prescribed dose. If you miss a dose, take your next dose at your usual time.
· Call your healthcare provider if the dose you are taking does not control your pain.
· If you have been taking acetaminophen and codeine phosphate tablets regularly, do not stop taking acetaminophen and codeine phosphate tablets without talking to your healthcare provider.
· Dispose of expired, unwanted, or unused acetaminophen and codeine phosphate tablets by taking your drug to an authorized DEA-registered collector or drug take-back program. If one is not available, you can dispose of acetaminophen and codeine phosphate tablets by mixing the product with dirt, cat litter, or coffee grounds; placing the mixture in a sealed plastic bag, and throwing the bag in your trash. Visit www.fda.gov/drugdisposal for additional information on disposal of unused medicines.

While taking acetaminophen and codeine phosphate tablets DO NOT:
· Drive or operate heavy machinery, until you know how acetaminophen and codeine phosphate tablets affect you. Acetaminophen and codeine phosphate tablets can make you sleepy, dizzy, or lightheaded.
· Drink alcohol or use prescription or over-the-counter medicines that contain alcohol. Using products containing alcohol during treatment with acetaminophen and codeine phosphate tablets may cause you to overdose and die.

The possible side effects of acetaminophen and codeine phosphate tablets:
· constipation, nausea, sleepiness, vomiting, tiredness, headache, dizziness, abdominal pain. Call your healthcare provider if you have any of these symptoms and they are severe.
Get emergency medical help or call 911 right away if you have:
· trouble breathing, shortness of breath, fast heartbeat, chest pain, swelling of your face, tongue, or throat, extreme drowsiness, light-headedness when changing positions, feeling faint, agitation, high body temperature, trouble walking, stiff muscles, or mental changes such as confusion.
These are not all the possible side effects of acetaminophen and codeine phosphate tablets. Call your healthcare provider for medical advice about side effects. You may report side effects to FDA at 1-800-FDA-1088. For more information go to dailymed.nlm.nih.gov.

This Medication Guide has been approved by the U.S. Food and Drug Administration.

Revised: 12/2025

Repackaged By / Distributed By: RemedyRepack Inc.

625 Kolter Drive, Indiana, PA 15701

(724) 465-8762

PACKAGE LABEL

DRUG: ACETAMINOPHEN AND CODEINE PHOSPHATE

GENERIC: acetaminophen and codeine phosphate

DOSAGE: TABLET

ADMINSTRATION: ORAL

NDC: 70518-2764-0

NDC: 70518-2764-1

COLOR: blue

SHAPE: ROUND

SCORE: No score

SIZE: 12 mm

IMPRINT: W243

PACKAGING: 30 in 1 BLISTER PACK

PACKAGING: 30 in 1 BLISTER PACK

ACTIVE INGREDIENT(S):

- CODEINE PHOSPHATE 60mg in 1
- ACETAMINOPHEN 300mg in 1

INACTIVE INGREDIENT(S):

- CELLULOSE, MICROCRYSTALLINE
- CROSCARMELLOSE SODIUM
- SILICON DIOXIDE
- MAGNESIUM STEARATE
- STARCH, CORN
- POVIDONE
- CROSPOVIDONE
- STEARIC ACID
- FD&C BLUE NO. 1